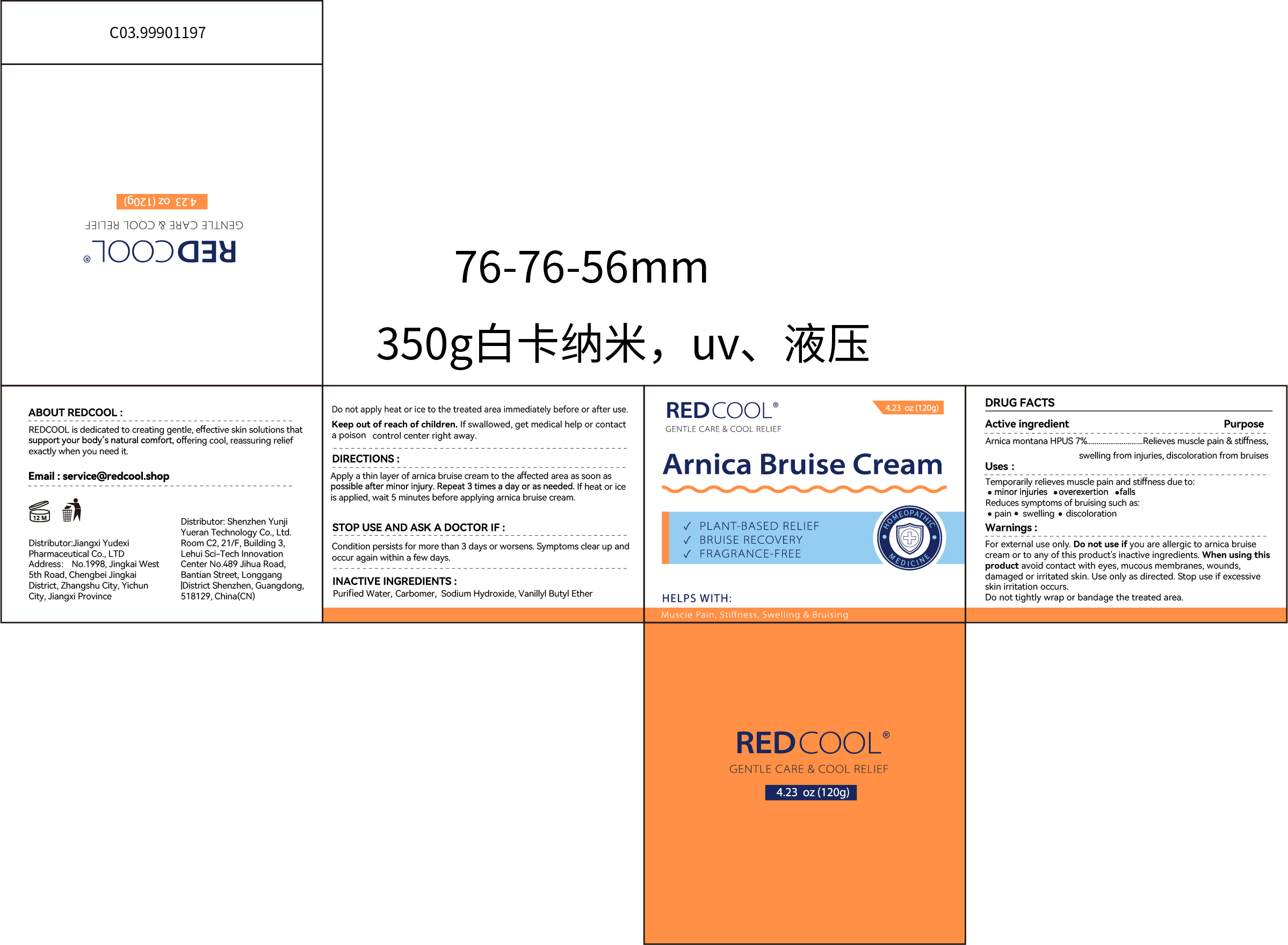 DRUG LABEL: REDCOOL Arnica Bruise
NDC: 85248-026 | Form: CREAM
Manufacturer: Jiangxi Zhongletang Pharmaceuticals Co.,Ltd.
Category: otc | Type: HUMAN OTC DRUG LABEL
Date: 20260129

ACTIVE INGREDIENTS: ARNICA MONTANA 7 g/100 g
INACTIVE INGREDIENTS: WATER; VANILLYL BUTYL ETHER; SODIUM HYDROXIDE; CARBOMER

85248-026

Active Ingredient

Arnica montana HPUS 7%

Purpose

Relieves muscle pain & stiffness，swelling from injuries, discoloration from bruises

Use

Temporarily relieves muscle pain and stiffness due to: ·cminor injuries ·overexertion ·falls Reduces symptoms of bruising such as: ·Pain·Swelling ·discoloration

Warnings

For external use only

Do not use if you are allergic to arnica bruise cream or to any of this product's inactive ingredients.

When Using

When using this product avoid contact with eyes, mucous membranes, wounds，damaged or irritated skin.Use only as directed .Stop use if excessive skin irritation occurs.
Do not tightly wrap or bandage the treated area. Do not apply heat or ice to the treated area immediately before or after use.

Stop Use

Condition persists for more than 3 days or worsens, Symptoms clear up and occur again within a few days.

Ask Doctor

Condition persists for more than 3 days or worsens, Symptoms clear up and occur again within a few days.

Keep Oot Of Reach Of Children

lf swallowed, get medical help or contact a Poison control center right away.

Directions

Apply a thin layer of arnica bruise cream to the affected area as soon as possible after minor injury. Repeat 3 times a day or as needed.lf heat or ice is applied, wait 5 minutes before applying arnica bruise cream.

Inactive ingredients

Purified water,Carbomer.Sodium Hydroxide, Vanilly Butyl Ether